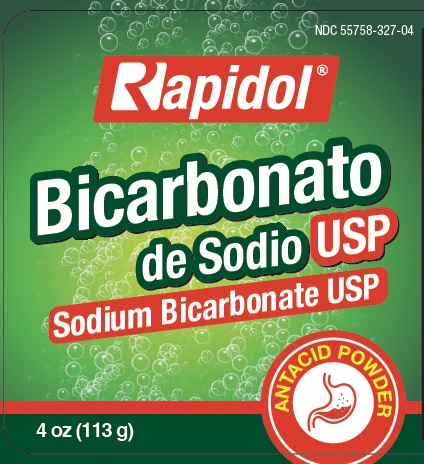 DRUG LABEL: Rapidol Sodium Bicarbonate
NDC: 55758-319 | Form: POWDER
Manufacturer: Pharmadel LLC
Category: otc | Type: HUMAN OTC DRUG LABEL
Date: 20251204

ACTIVE INGREDIENTS: SODIUM BICARBONATE 2.6 g/2.6 g

Rapidol Sodium Bicarbonate Antacid Powder (WP)(DA)

Active Ingredient & Purposes

Active ingredient (in each ½ teaspoon) | Purpose
Sodium bicarbonate 2,616 mg......................................................................................................... | Antacid

Uses For the relief of an upset stomach associated with these symptoms

- heatburn
- sour stomach
- acid indigestion

Warnings

Stomach Waring: To avoid serious injury, do not take powder until it is completely dissolved. It is very important not to take this product when overly full from food or drink. Consult a doctor if severe stomach pain occurs after taking this product.

Do not use

- the maximum daily dosage of this product for more than 2 weeks, except under the advice and supervision of a doctor
- this product except under advice and supervision of a physician if you are allergic to milk or milk products

When using this product

- may cause constipation
- may have laxative effect

Ask a doctor or pharmacist before use if you are

- presently taking a prescription drug. Antacids may interact with certain prescription drugs.

Ask a doctor before use if you have

- a sodium-restricted diet

If pregnant or breast-feeding,

ask a health professional before use.

KEEP OUT OF REACH OF CHILDREN.

In case of an accidental overdose, seek professional assistance or contact a Poison Control center right away.

Directions

- do not take more than your “ maximum daily dosage for your age group” in a 24-hour period. See Warnings.
- take a ½ teaspoon in a 4 fl. oz. (½ a glass) of water every 2 hours up to the maximum daily dosage or as directed by a doctor
- dissolve completely in water before drinking

age | maximum daily dosage
adults 60 years of age and over | ½ teaspoon, 3 times a day
adults under 60 and children 12 years of age and over | ½ teaspoon, 6 times a day
children under 12 years of age | do not use

Other information

- each ½ teaspoonful contains: sodium 716 mg
- store in cool dry place below 77ºF
- do not use if seal under cap is torn, broken or missing

INACTIVE INGREDIENT

None

Questions & comments?

PHARMADEL LLC.

New Castle, DE, 19720

+1-866-359-3478

www.pharmadel.com

Prinicpal Display Panel

55758-327-04

4 Oz